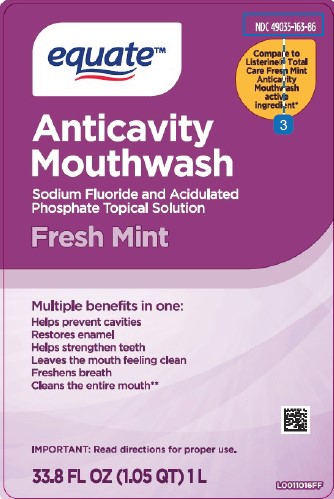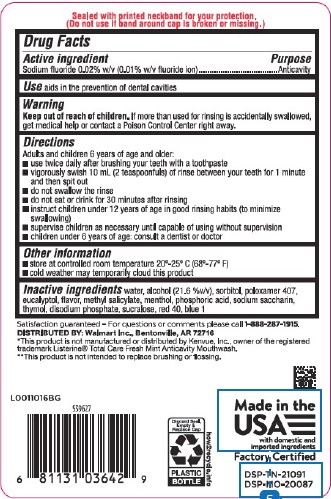 DRUG LABEL: Anticavity
NDC: 49035-163 | Form: MOUTHWASH
Manufacturer: Walmart Inc.
Category: otc | Type: HUMAN OTC DRUG LABEL
Date: 20260227

ACTIVE INGREDIENTS: SODIUM FLUORIDE 0.1 mg/1 mL
INACTIVE INGREDIENTS: WATER; ALCOHOL; SORBITOL; POLOXAMER 407; EUCALYPTOL; METHYL SALICYLATE; MENTHOL; PHOSPHORIC ACID; SACCHARIN SODIUM; THYMOL; SODIUM PHOSPHATE, DIBASIC, ANHYDROUS; SUCRALOSE; FD&C RED NO. 40; FD&C BLUE NO. 1

Equate 163.005/163AG
Anticavity Fluoride Rinse

Tamper Evident Statement

Sealed with printed neckband for your protection.

(Do not use if band around cap is broken or missing.)

Active ingredient

Sodium Fluoride 0.02% (0.01% w/v fluoride ion)

Purpose

Anticavity

Use

aids in the prevention of dental cavities

Warning

for this product

Keep out of reach of children.

If more than used for rinsing is accidentally swallowed, get medical help or contact a Poison Control Center right away.

Directions

Adults and children 6 years of age and older:

- use twice daily after brushing your teeth with a toothpaste
- vigorously swish 10 ml (2 teaspoonfuls) of rinse between your teeth for 1 minute then spit out
- do not swallow the rinse
- do not eat or drink for 30 minutes after rinsing
- instruct children under 12 years of age in good rinsing habits (to minimize swallowing)
- supervise children as necessary until capable of using without supervision
- children under 6 years of age: consult a dentist or doctor

Other information

- store at controlled room temperature 20⁰ - 25⁰C (68⁰ - 77⁰F)
- cold weather may temporarily cloud this product

Inactive ingredients

water, alcohol (21.6 %v/v), sorbitol, poloxamer 407, eucalyptol, flavor, methyl salicylate, menthol, phosphoric acid, sodium saccharin, thymol, disodium phosphate, sucralose, red 40, blue 1

Questions

Satisfaction guaranteed - For questions or comments please call 1-888-287-1915.

Adverse reaction

DISTRIBUTED BY: Walmart Inc. Bentonville, AR 72716

Made in the USA with domestic imported ingredients

Factory Certified

Discard Seal, Empty & Replace Cap

PLASTIC BOTTLE

how2recycle.info

Disclaimers

*This product is not manufactured or distributed by Kenvue, Inc., owner of the registered trademark Listerine® Total Care Fresh Mint Anticavity Mouthwash.

**This product is not intended to replace brushing or flossing.

Principal display panel

equate™

NDC 49035-163-86

Compare to Listerine®Total Care Fresh Mint Anticavity Mouthwash Active Ingredient*

Anticavity Mouthwash

Sodium Fluoride and Acidulated Phosphate Topical Solution

Fresh Mint

Multiple benefits in one:

Helps prevent cavities
Restores enamel
Helps strengthen teeth
Helps kill bad breath germs
Freshens breath
Cleans the entire mouth**

IMPORTANT: Read directions for proper use.

33.8 FL OZ (1.05 QT) 1 L